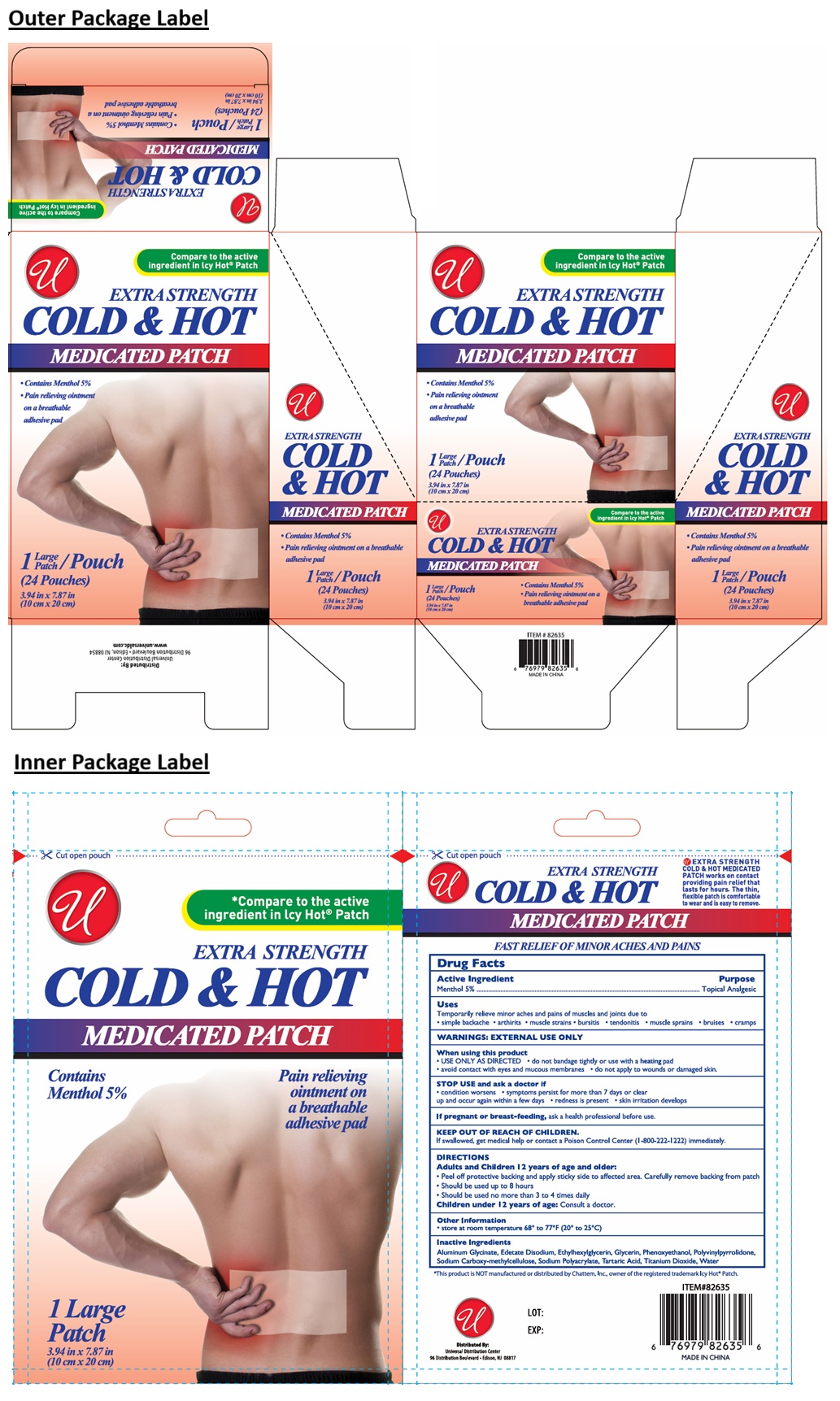 DRUG LABEL: COLD AND HOT MEDICATED LARGE
NDC: 52000-421 | Form: PATCH
Manufacturer: Universal Distribution Center LLC
Category: otc | Type: HUMAN OTC DRUG LABEL
Date: 20250929

ACTIVE INGREDIENTS: MENTHOL, UNSPECIFIED FORM 0.05 g/1 g
INACTIVE INGREDIENTS: DIHYDROXYALUMINUM AMINOACETATE ANHYDROUS; EDETATE DISODIUM; ETHYLHEXYLGLYCERIN; GLYCERIN; PHENOXYETHANOL; POVIDONE, UNSPECIFIED; CARBOXYMETHYLCELLULOSE SODIUM, UNSPECIFIED; SODIUM POLYACRYLATE (2500000 MW); TARTARIC ACID; TITANIUM DIOXIDE; WATER

COLD & HOT MEDICATED LARGE PATCH

Active Ingredient

Menthol 5%

Purpose

Topical Analgesic

Uses

Temporarily relieve minor aches and pains of muscles and joints due to
• simple backache • arthritis • muscle strains • bursitis • tendonitis • muscle sprains • bruises • cramps

WARNINGS:

EXTERNAL USE ONLY

When using this product
• USE ONLY AS DIRECTED • do not bandage tightly or use with a heating pad
• avoid contact with eyes and mucous membranes • do not apply to wounds or damaged skin.

STOP USE and ask a doctor if
• condition worsens • symptoms persist for more than 7 days or clear up and occur again within a few days • redness is present • skin irritation develops

If pregnant or breast-feeding, ask a health professional before use.

KEEP OUT OF REACH OF CHILDREN.
If swallowed, get medical help or contact a Poison Control Center (1-800-222-1222) immediately.

DIRECTIONS

Adults and Children 12 years of age and older:
• Peel off protective backing and apply sticky side to affected area. Carefully remove backing from patch
• Should be used up to 8 hours
• Should be used no more than 3 to 4 times daily
Children under 12 years of age: Consult a doctor.

Other Information

• store at room temperature 68° to 77°F (20° to 25°C)

Inactive Ingredients

Aluminum Glycinate, Edetate Disodium, Ethylhexylglycerin, Glycerin, Phenoxyethanol, Polyvinylpyrrolidone, Sodium Carboxy-methylcellulose, Sodium Polyacrylate, Tartaric Acid, Titanium Dioxide, Water

*Compare to the active ingredient in Icy Hot® Patch

EXTRA STRENGTH

Contains Menthol 5%

Pain relieving ointment on a breathable adhesive pad

EXTRA STRENGTH COLD & HOT MEDICATED PATCH works on contact providing pain relief that lasts for hours. The thin, flexible patch is comfortable to wear and is easy to remove.

FAST RELIEF OF MINOR ACHES AND PAINS

*This product is NOT manufactured or distributed by Chattem Inc., owner of the registered trademark Icy Hot® Patch.

Distributed By:
Universal Distribution Center
96 Distribution Boulevard • Edison, NJ 08817

MADE IN CHINA

www.universaldc.com